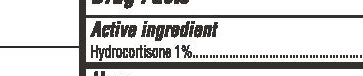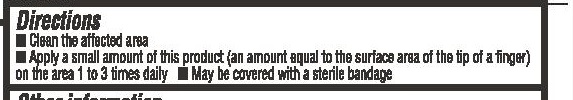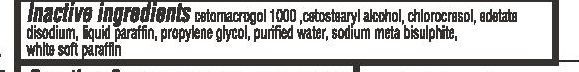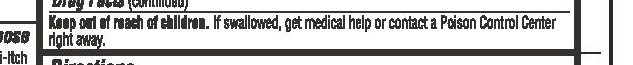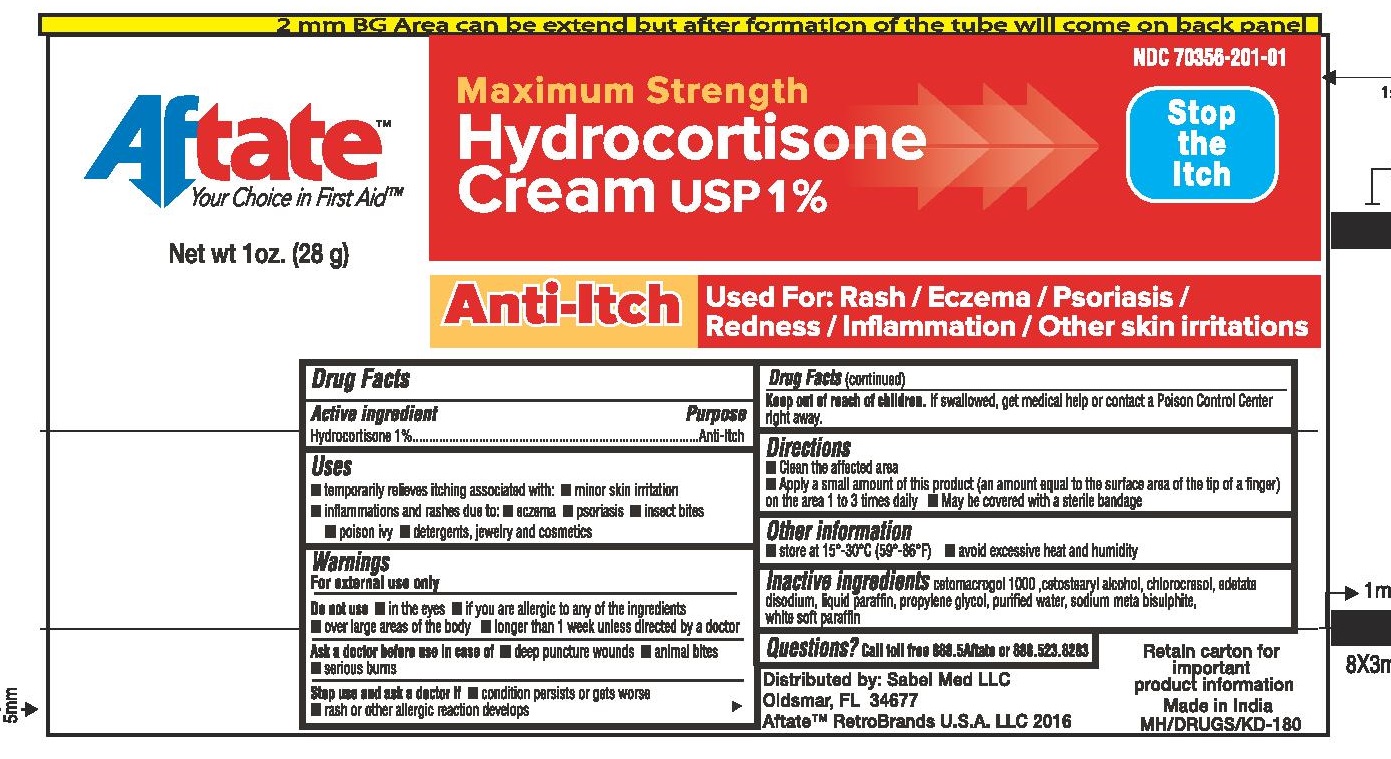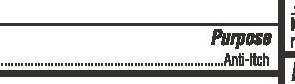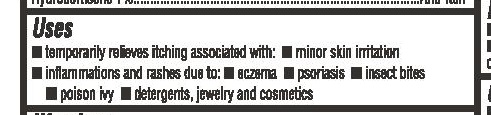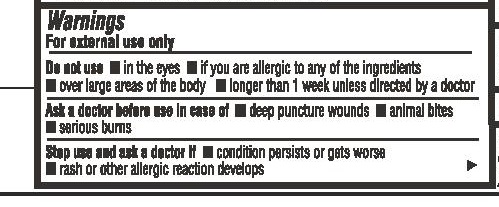 DRUG LABEL: Aftate Hydrocortisone Cream
NDC: 70356-201 | Form: CREAM
Manufacturer: Sabel Med LLC
Category: otc | Type: HUMAN OTC DRUG LABEL
Date: 20160331

ACTIVE INGREDIENTS: HYDROCORTISONE ACETATE 1 g/100 g
INACTIVE INGREDIENTS: WATER; CETOSTEARYL ALCOHOL; PROPYLENE GLYCOL; MINERAL OIL; CETETH-20; EDETATE DISODIUM; CHLOROCRESOL; SODIUM METABISULFITE; PETROLATUM

Hydrocortisone Cream USP 1% 1 oz